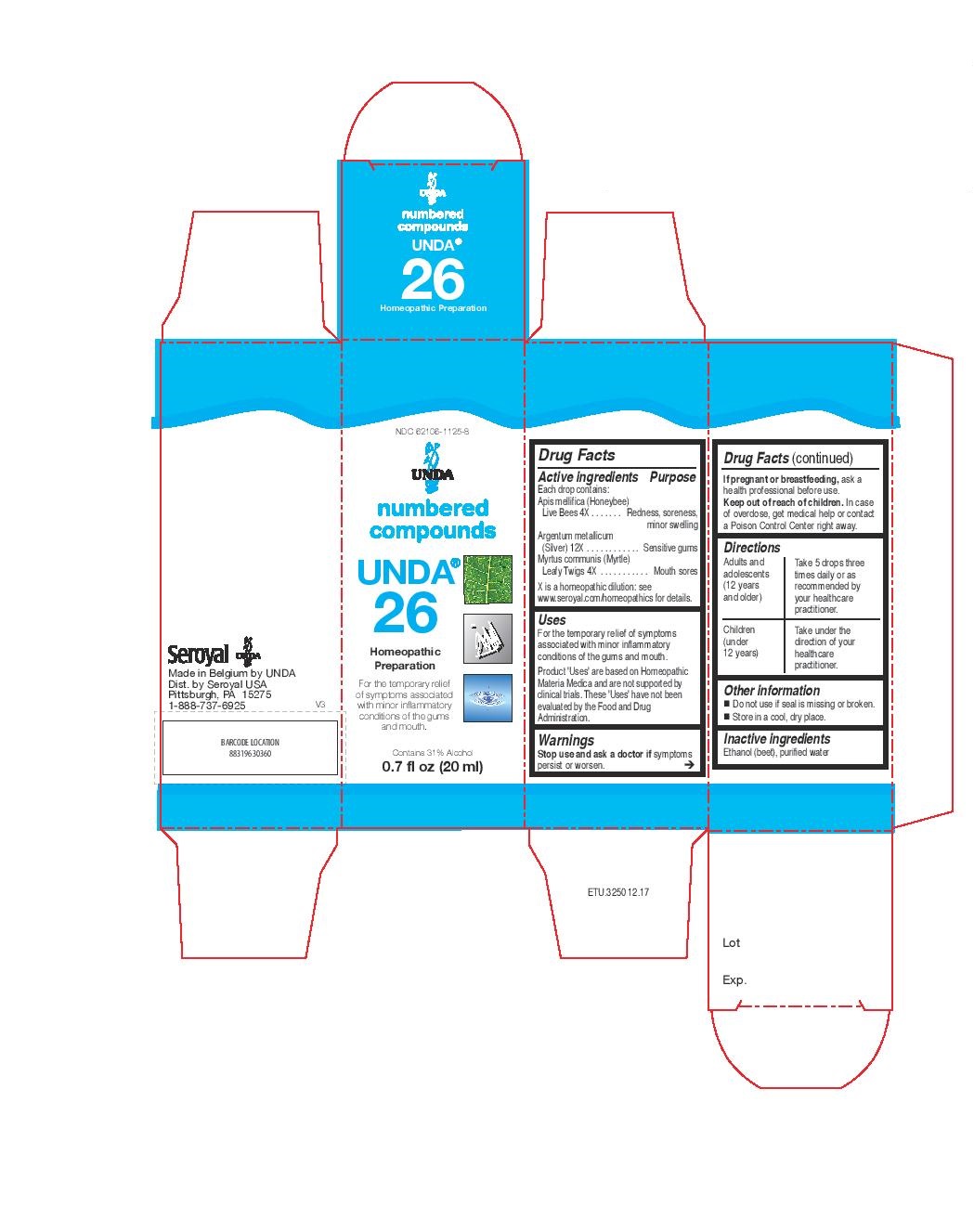 DRUG LABEL: Unda 26
NDC: 62106-1125 | Form: LIQUID
Manufacturer: Seroyal USA
Category: homeopathic | Type: HUMAN OTC DRUG LABEL
Date: 20221109

ACTIVE INGREDIENTS: MYRTUS COMMUNIS TOP 4 [hp_X]/20 mL; APIS MELLIFERA 4 [hp_X]/20 mL; SILVER 12 [hp_X]/20 mL
INACTIVE INGREDIENTS: ALCOHOL; WATER

UNDA 26

Active ingredients
Each drop contains:
Apis mellifica (Honeybee) Live Bees 4X
Argentum metallicum (Silver) 12X
Myrtus communis (Myrtle) Leafy Twigs 4X

Uses
For the temporary relief of symptoms associated with minor inflammatory conditions of the gums and mouth.

Warnings

Stop use and ask a doctor if symptoms persist or worsen.
If pregnant or breastfeeding, ask a health professional before use.

Keep out of reach of children.

In case of overdose, get medical help or contact a
Poison Control Center right away.

PREGNANCY OR BREAST FEEDING

If pregnant or breastfeeding, ask a health professional before use.

Keep out of reach of children.

OVERDOSAGE

In case of overdose, get medical help or contact a

Poison Control Center right away.

Stop use and ask a doctor if symptoms persist or worsen.

Inactive ingredients
Ethanol (beet), purified water

Other information
Do not use if seal is missing or broken.
Store in a cool, dry place.

Directions

Adults and adolescents (12 years and older)

Take 5 drops three times daily or as recommended by your healthcare practitioner.

Children (under 12 years)

Take under the direction of your healthcare practitioner.

Uses
For the temporary relief of symptoms associated with minor inflammatory conditions of the gums and mouth.

Directions

Adults and adolescents (12 years and older)

Take 5 drops three times daily or as recommended by your healthcare practitioner.

Children (under 12 years)

Take under the direction of your healthcare practitioner.

PACKAGE LABEL

NDC 62106-1125-8

UNDA

numbered compounds

UNDA 26

Homeopathic Preparation

For the temporary relief of symptoms

associated with minor inflammatory

conditions of the gums and mouth.

Contains 31% Alcohol
0.7 fl oz (20 ml)